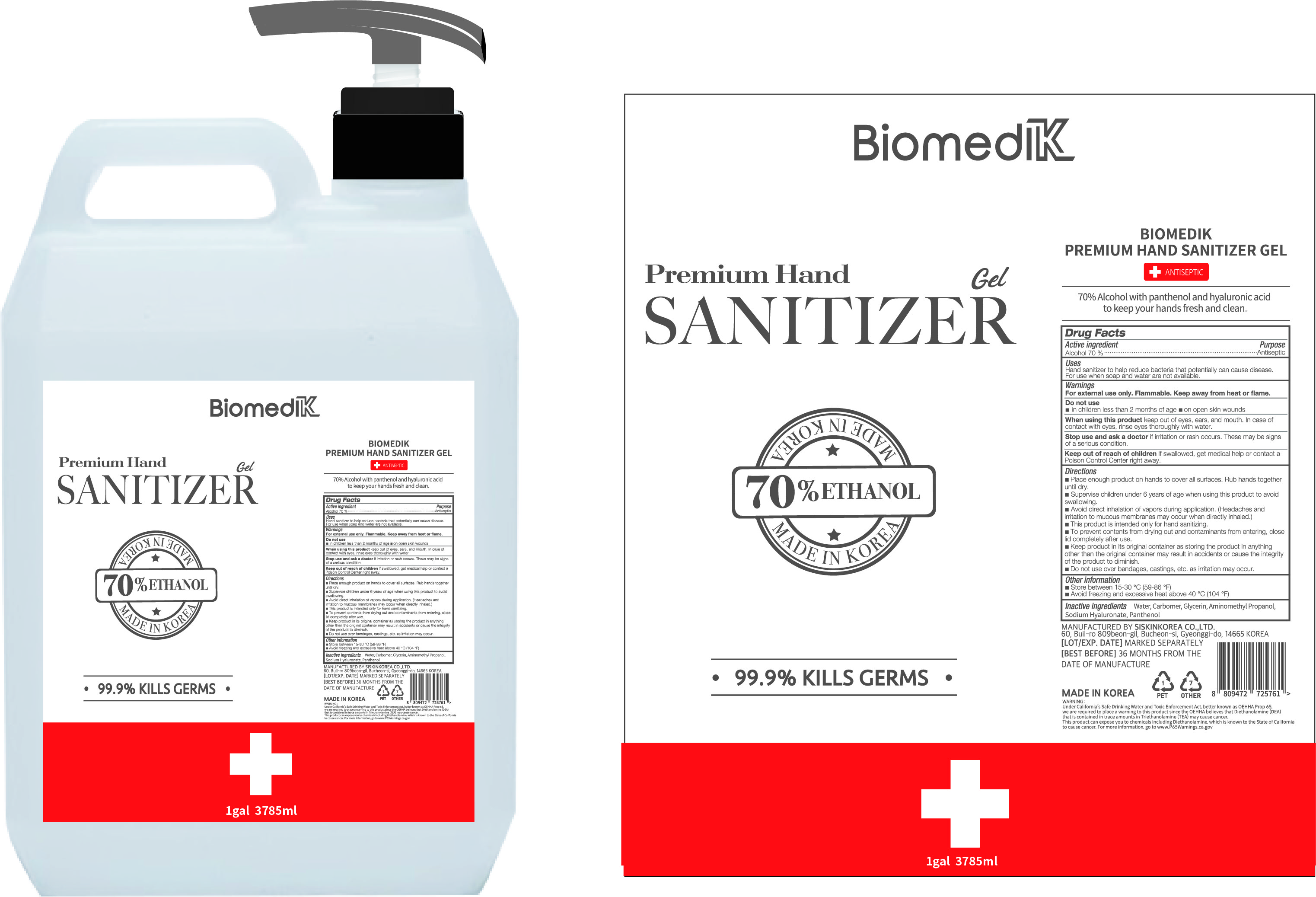 DRUG LABEL: BIOMEDIK Premium HAND SANITIZER Gel
NDC: 74514-3785 | Form: GEL
Manufacturer: SISKINKOREA CO.,LTD.
Category: otc | Type: HUMAN OTC DRUG LABEL
Date: 20200531

ACTIVE INGREDIENTS: ALCOHOL 2649.5 mL/3785 mL
INACTIVE INGREDIENTS: GLYCERIN; AMINOMETHYLPROPANOL; PANTHENOL; WATER; HYALURONATE SODIUM; CARBOMER HOMOPOLYMER, UNSPECIFIED TYPE

BIOMEDIK Premium Hand Sanitizer Gel [74514-3785-1] 3785 mL, Bottle+Pump